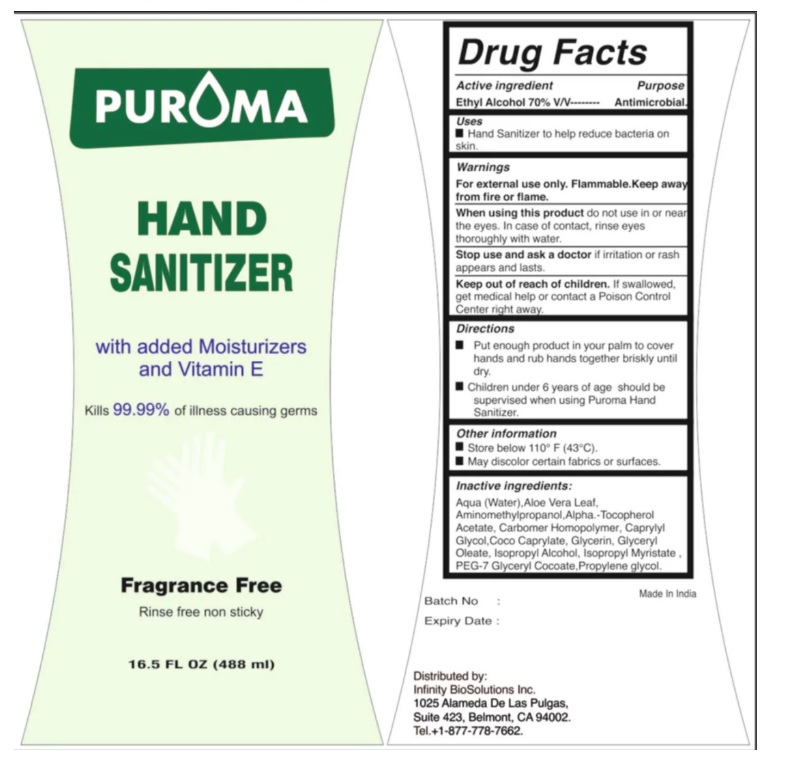 DRUG LABEL: PUROMA Hand Sanitizer Fragrance Free
NDC: 80948-009 | Form: LIQUID
Manufacturer: ZENITH MICRO CONTROL
Category: otc | Type: HUMAN OTC DRUG LABEL
Date: 20231214

ACTIVE INGREDIENTS: ALCOHOL 70 mL/100 mL
INACTIVE INGREDIENTS: WATER; ISOPROPYL ALCOHOL; GLYCERIN; ISOPROPYL MYRISTATE; .ALPHA.-TOCOPHEROL ACETATE; CARBOMER HOMOPOLYMER, UNSPECIFIED TYPE; CAPRYLYL GLYCOL; AMINOMETHYLPROPANOL; ALOE VERA LEAF; PROPYLENE GLYCOL; COCO-CAPRYLATE; GLYCERYL OLEATE; PEG-7 GLYCERYL COCOATE

Active ingredient

Ethyl alcohol 70% V/V

Purpose

Antimicrobial

Uses

Hand Sanitizer to help reduce bacteria on skin.

Warnings

For external use only. Flammable. Keep away from fire or flame.

When using this product do not use in or near the eyes. In case of contact, rinse eyes thoroughly with water.

Stop use and ask a doctor if irritation or rash appears and lasts.

Keep out of reach of children

If swallowed, get medical help or contact a Poison Control Center right away.

Directions

Put enough product in your palm to cover hands and rub hands together briskly until dry.
Children under 6 years of age should be supervised when using Puroma Hand Sanitizer.

Inactive ingredients

Water, Aminomethylpropanol, Aloe Vera Leaf, Isopropyl Alcohol, Glycerin, Isopropyl Myristate, Alpha.-Tocopherol Acetate , Carbomer Homopolymer , Caprylyl Glycol, Coco Caprylate. Glyceryl Oleate, PEG-7 Glyceryl Cocoate, Propylene Glycol.

Other information

• Store below 110°F (430°C)
• May discolor certain fabrics or surfaces